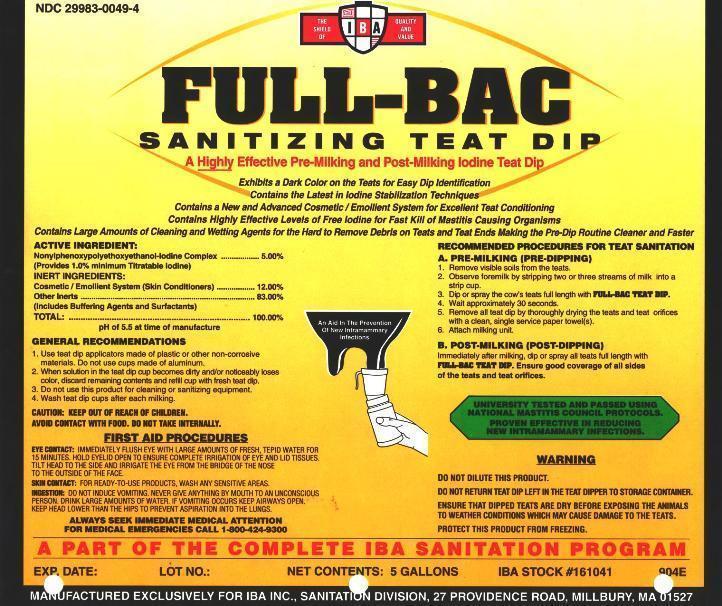 DRUG LABEL: FULL-BAC
NDC: 29983-0049 | Form: SOLUTION
Manufacturer: IBA
Category: animal | Type: OTC ANIMAL DRUG LABEL
Date: 20220719

ACTIVE INGREDIENTS: IODINE 10 g/1 L

FULL-BAC SANITIZING TEAT DIP A Highly Effective Pre-Milking and Post-Milking Iodine Teat Dip Exhibits a Dark Color on the Teats for Easy Dip Identification Contains the Latest in Iodine Stabilization Techniques Contains a New and Advanced Cosmetic/Emollient System for Excellent Teat Conditioning Contains Highly Effective Levels of Free Iodine for Fast Kill of Mastitis Causing Organisms Contains Large Amounts of Cleaning and Wetting Agents for the Hard to Remove Debris on Teats and Teat Ends Making the Pre-Dip Routine Cleaner and Faster

ACTIVE INGREDIENT:

Nonylphenoxypolyethoxyethanol-Iodine Complex.....5.0%
(Provides a 1.0% minimum of Titratable Iodine)
INERT INGREDIENTS
COSMETIC/EMOLLIENT SYSTEM (SKIN CONDITIONERS).......12.00%
Other Inerts.....83.00%
(Includes Buffering Agents and Surfactants)
Total.................100%
pH of 5.5 at time of manufacture

INDICATIONS AND USAGE

GENERAL RECOMMENDATIONS
1. Use teat dip applicators made of plastic or other non-corrosive materials. Do not use cups made of aluminum.
2. When solution in the teat dip cup becomes dirty and/or noticeably loses color, discard remaining contents and refill cup with fresh teat dip.
3. Do not use this product for cleaning or sanitizing equipment.
4. Wash teat dip cups after each milking.
RECOMMENDED PROCEDURES FOR TEAT SANITATION
A. PRE-MILKING (PRE-DIPPING)
1. REMOVE VISIBLE SOILS FROM THE TEATS.
2. OBSERVE FOREMILK BY STRIPPING TWO OR THREE STREAMS OF MILK INTO A STRIP CUP.
3. DIP OR SPRAY THE COW'S TEATS FULL LENGTH WITH FULL-BAC TEAT DIP.
4. WAIT APPROXIMATELY 30 SECONDS.
5. REMOVE ALL TEAT DIP BY THOROUGHLY DRYING THE TEATS AND TEAT ORIFICES WITH A CLEAN, SINGLE SERVICE PAPER TOWEL(S).
6. ATTACH MILKING UNIT.
B. POST-MILKING (POST -DIPPING)
Immediately after milking dip all teats full length with FULL-BAC Teat Dip. Ensure good coverage of all sides of the teats and teat orifices.

UNIVERSITY TESTED AND PASSED USING NATIONAL MASTITIS COUNCIL PROTOCOLS.

PROVEN EFFECTIVE IN REDUCING NEW INTRAMAMMARY INFECTIONS.

A PART OF THE COMPLETE IBA SANITATION PROGRAM

WARNINGS AND PRECAUTIONS

EYE CONTACT: IMMEDIATELY FLUSH EYE WITH LARGE AMOUNTS OF FRESH, TEPID WATER FOR 15 MINUTES. HOLD EYELID OPEN TO ENSURE COMPLETE IRRIGATION OF EYE AND LID TISSUES. TILT HEAD TO THE SIDE AND IRRIGATE THE EYE FROM THE BRIDGE OF THE NOSE TO THE OUTSIDE OF THE FACE.
SKIN CONTACT: FOR READY-TO-USE, WASH ANY SENSITIVE AREAS.
INGESTION: DO NOT INDUCE VOMITING. NEVER GIVE ANYTHING BY MOUTH TO AN UNCONSCIOUS PERSON. DRINK LARGE AMOUNTS OF WATER. IF VOMITING OCCURS KEEP AIRWAYS OPEN. KEEP HEAD LOWER THAN THE HIPS TO PREVENT ASPIRATION INTO THE LUNGS.
ALWAYS SEEK IMMEDIATE MEDICAL ATTENTION

FOR MEDICAL EMERGENCIES CALL 1-800-424-9300